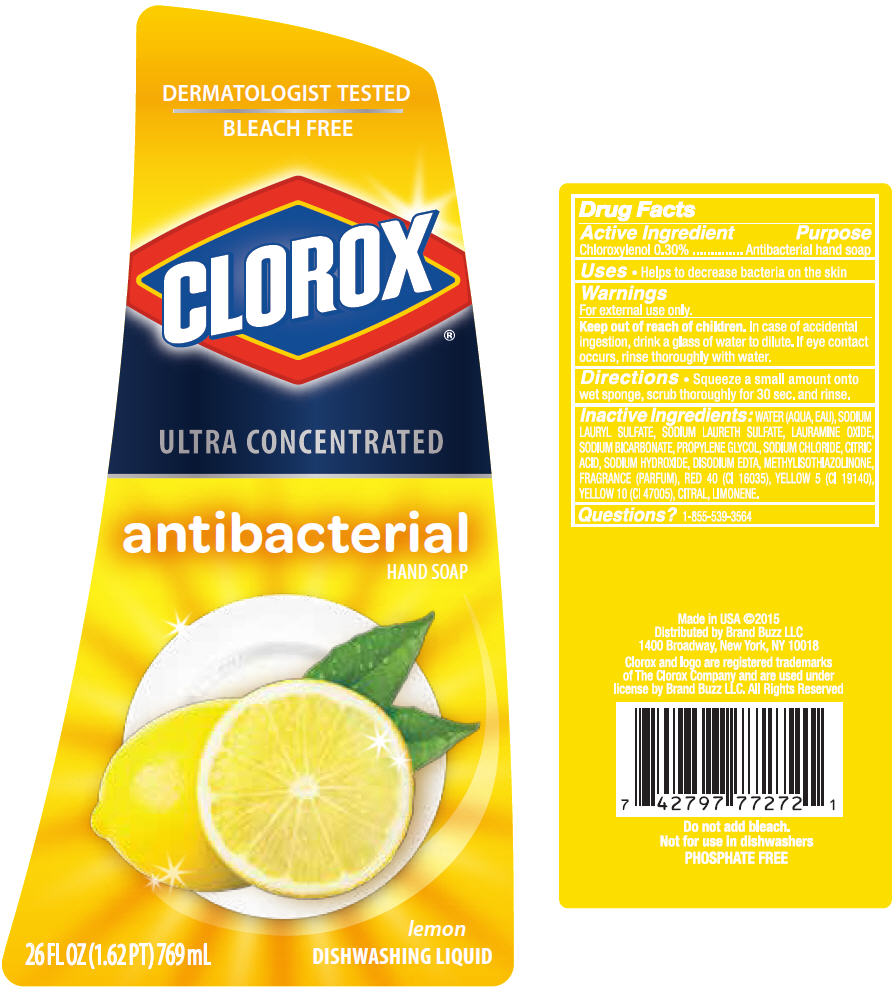 DRUG LABEL: Clorox Lemon Dish
NDC: 69540-0009 | Form: SOAP
Manufacturer: Brand Buzz
Category: otc | Type: HUMAN OTC DRUG LABEL
Date: 20150123

ACTIVE INGREDIENTS: Chloroxylenol 0.003 g/1 mL
INACTIVE INGREDIENTS: Water; Sodium Lauryl Sulfate; Sodium Laureth-3 Sulfate; Lauramine Oxide; Sodium Bicarbonate; Propylene Glycol; Sodium Chloride; Citric Acid Monohydrate; Sodium Hydroxide; Methylisothiazolinone; Edetate Disodium; FD&C Red No. 40; FD&C Yellow No. 5; D&C Yellow NO. 10; Citral

Clorox® Lemon Dish Soap

Drug Facts

Active Ingredient

Chloroxylenol 0.30%

Purpose

Antibacterial hand soap

Uses

- Helps to decrease bacteria on the skin

Warnings

For external use only.

Keep out of reach of children. In case of accidental ingestion, drink a glass of water to dilute. If eye contact occurs, rinse thoroughly with water.

Directions

- Squeeze a small amount onto wet sponge, scrub thoroughly for 30 sec. and rinse.

Inactive Ingredients

WATER (AQUA, EAU), SODIUM LAURYL SULFATE, SODIUM LAURETH SULFATE, LAURAMINE OXIDE, SODIUM BICARBONATE, PROPYLENE GLYCOL, SODIUM CHLORIDE, CITRIC ACID, SODIUM HYDROXIDE, DISODIUM EDTA, METHYLISOTHIAZOLINONE, FRAGRANCE (PARFUM), RED 40 (CI 16035), YELLOW 5 (CI 19140), YELLOW 10 (CI 47005), CITRAL, LIMONENE.

Questions?

1-855-539-3564

Distributed by Brand Buzz LLC
1400 Broadway, New York, NY 10018

PRINCIPAL DISPLAY PANEL - 769 mL Bottle Label

DERMATOLOGIST TESTED
BLEACH FREE

CLOROX®

ULTRA CONCENTRATED

antibacterial
HAND SOAP

lemon
DISHWASHING LIQUID

26 FL OZ (1.62 PT) 769 mL